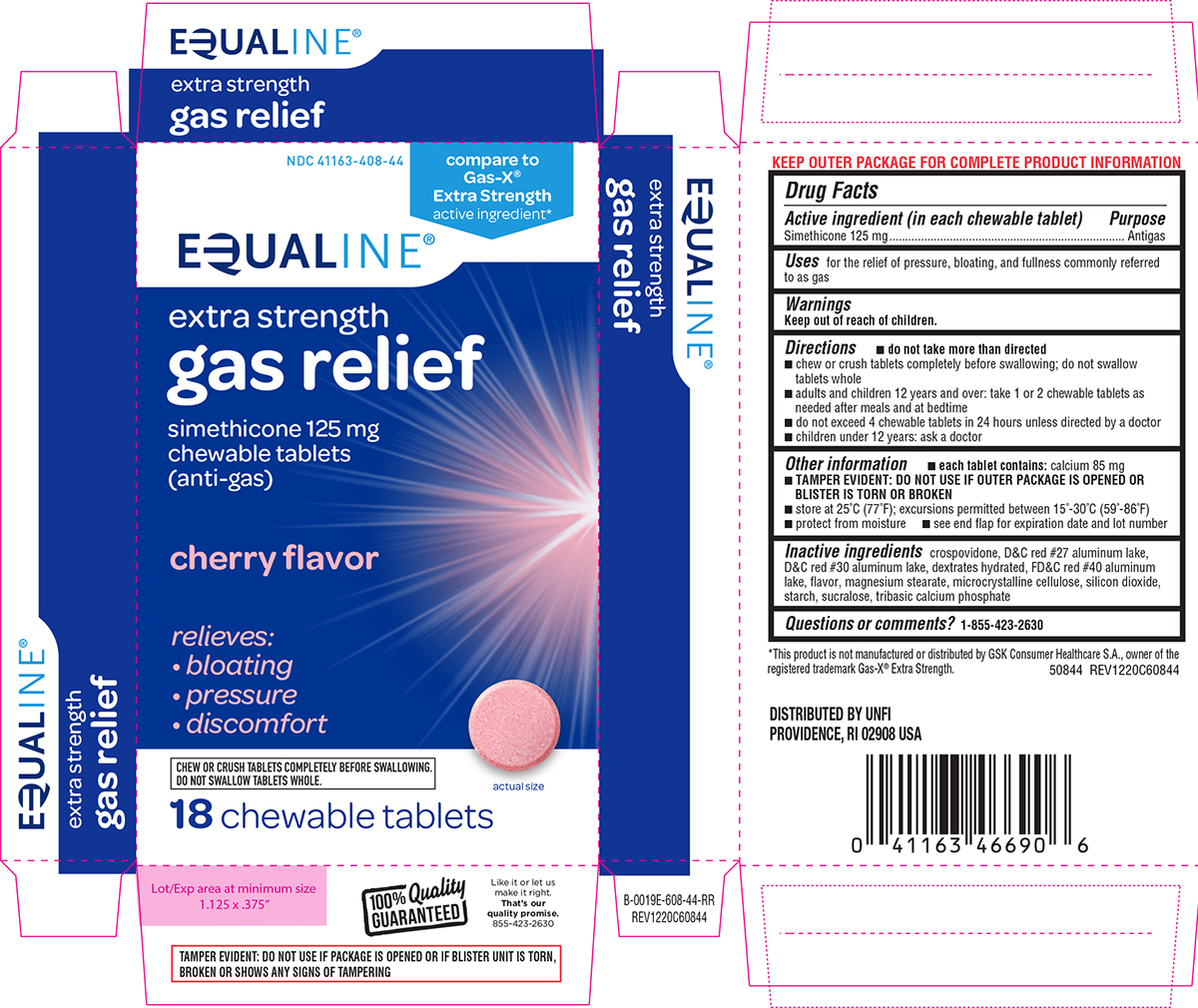 DRUG LABEL: gas relief
NDC: 41163-408 | Form: TABLET, CHEWABLE
Manufacturer: United Natural Foods, Inc. dba UNFI
Category: otc | Type: HUMAN OTC DRUG LABEL
Date: 20250510

ACTIVE INGREDIENTS: DIMETHICONE 125 mg/1 1
INACTIVE INGREDIENTS: CROSPOVIDONE, UNSPECIFIED; D&C RED NO. 27 ALUMINUM LAKE; D&C RED NO. 30 ALUMINUM LAKE; DEXTROSE MONOHYDRATE; FD&C RED NO. 40 ALUMINUM LAKE; MAGNESIUM STEARATE; MICROCRYSTALLINE CELLULOSE; SILICON DIOXIDE; STARCH, CORN; SUCRALOSE; TRIBASIC CALCIUM PHOSPHATE; DIMETHICONE 410

Equaline 44-608

Active ingredient (in each chewable tablet)

Simethicone 125 mg

Purpose

Antigas

Uses

for the relief of pressure, bloating, and fullness commonly referred to as gas

Directions

- do not take more than directed
- chew or crush tablets completely before swallowing; do not swallow tablets whole
- adults and children 12 years and over: take 1 or 2 chewable tablets as needed after meals and at bedtime
- do not exceed 4 chewable tablets in 24 hours unless directed by a doctor
- children under 12 years: ask a doctor

Other information

- each tablet contains: calcium 85 mg
- TAMPER EVIDENT: DO NOT USE IF OUTER PACKAGE IS OPENED OR BLISTER IS TORN OR BROKEN
- store at 25°C (77°F); excursions permitted between 15°-30°C (59°-86°F)
- protect from moisture
- see end flap for expiration date and lot number

Inactive ingredients

crospovidone, D&C red #27 aluminum lake, D&C red #30 aluminum lake, dextrates hydrated, FD&C red #40 aluminum lake, flavor, magnesium stearate, microcrystalline cellulose, silicon dioxide, starch, sucralose, tribasic calcium phosphate

Questions or comments?

1-855-423-2630

Principal display panel

NDC 41163-408-44

Compare to
Gas-X®
Extra Strength
active ingredient*

EQUALINE®

extra strength

gas relief
simethicone 125 mg
chewable tablets
(anti-gas)

cherry flavor

relieves:
•bloating
•pressure
•discomfort

CHEW OR CRUSH TABLETS COMPLETELY BEFORE SWALLOWING.
DO NOT SWALLOW TABLETS WHOLE.

actual size

18 chewable tablets

TAMPER EVIDENT: DO NOT USE IF PACKAGE IS OPENED OR IF BLISTER UNIT IS TORN,
BROKEN OR SHOWS ANY SIGNS OF TAMPERING

*This product is not manufactured or distributed by GSK Consumer Healthcare S.A., owner of the
registered trademark Gas-X® Extra Strength. 50844 REV1220C60844

DISTRIBUTED BY UNFI
PROVIDENCE, RI 02908 USA

Like it or let us
make it right.
That’s our
quality promise.
855-423-2630

Equaline 44-608